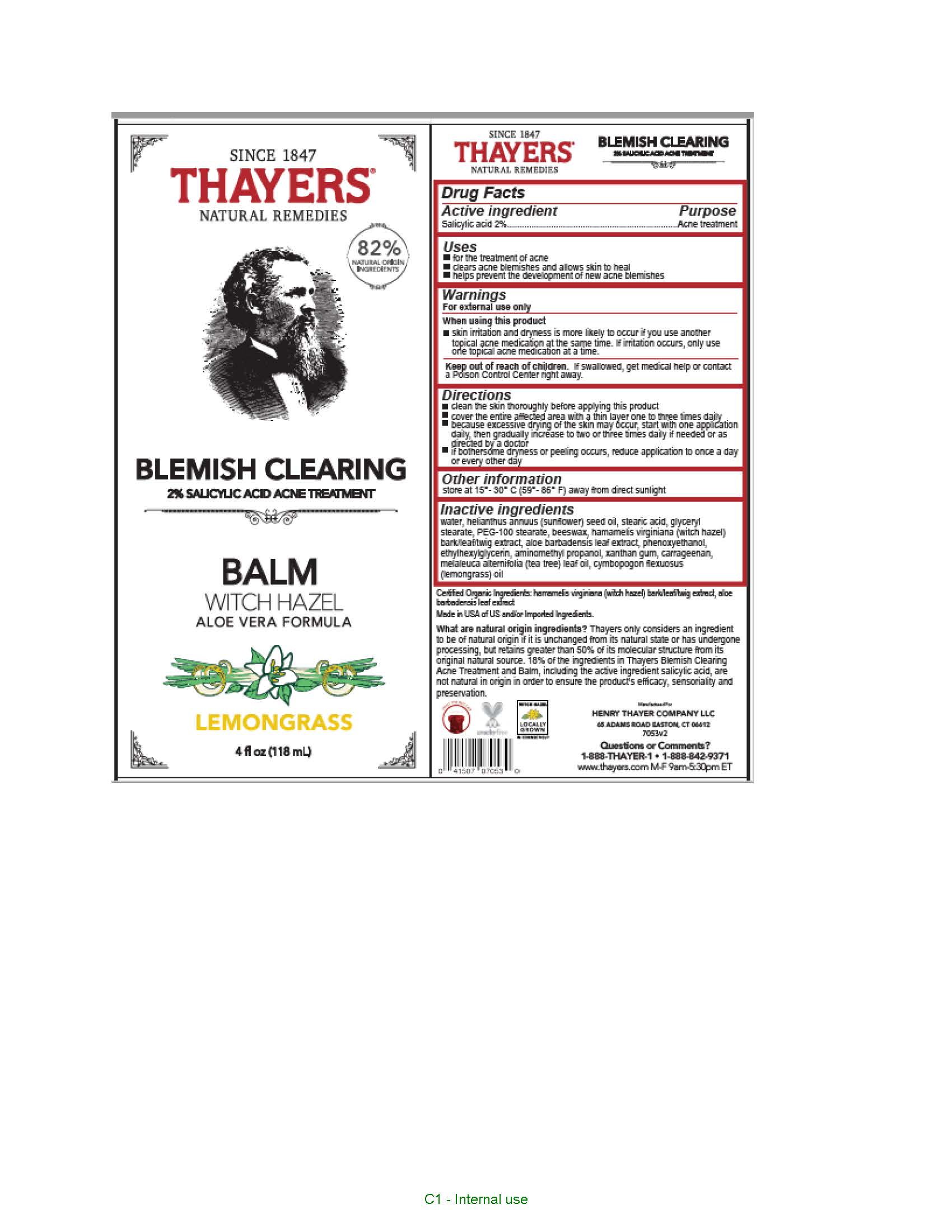 DRUG LABEL: Thayers Since 1847 Natural Remedies Blemish Clearing Witch Hazel Aloe Vera Formula Balm
NDC: 49967-530 | Form: GEL
Manufacturer: L'Oreal USA Products Inc
Category: otc | Type: HUMAN OTC DRUG LABEL
Date: 20241230

ACTIVE INGREDIENTS: SALICYLIC ACID 20 mg/1 mL
INACTIVE INGREDIENTS: WATER; SUNFLOWER OIL; STEARIC ACID; GLYCERYL DISTEARATE; PEG-100 STEARATE; YELLOW WAX; HAMAMELIS VIRGINIANA TOP; ALOE VERA LEAF; PHENOXYETHANOL; ETHYLHEXYLGLYCERIN; AMINOMETHYLPROPANOL; XANTHAN GUM; CARRAGEENAN; TEA TREE OIL

Drug Facts

Active ingredient

Salicylic acid 2%

Purpose

Acne treatment

Uses

• for the treatment of acne
• clears acne blemishes and allows skin to heal
• helps prevent the development of new acne blemishes

Warnings

For external use only

When using this product

skin irritation and dryness is more likely to occur if you use another topical acne medication at the same time. If irritation occurs, only use one topical acne medication at a time.

Keep out of reach of children.

If swallowed, get medical help or contact a Poison Control Center right away.

Directions

- clean the skin thoroughly before applying this product
- cover the entire affected area with a thin layer one to three times daily
- because excessive drying of the skin may occur, start with one application daily, then gradually increase to two or three times daily if needed or as directed by a doctor
- if bothersome dryness or peeling occurs, reduce application to once a day or every other day

Other information

store at 15°-30° C (59°-86° F) away from direct sunlight

Inactive ingredients

water, helianthus annuus (sunflower) seed oil, stearic acid, glyceryl stearate, PEG-100 stearate, beeswax, hamamelis virginiana (witch hazel)
bark/leaf/twig extract, aloe barbadensis leaf extract, phenoxyethanol, ethylhexylglycerin, aminomethyl propanol, xanthan gum, carrageenan,
melaleuca alternifolia (tea tree) leaf oil, cymbopogon flexuosus (lemongrass) oil